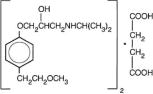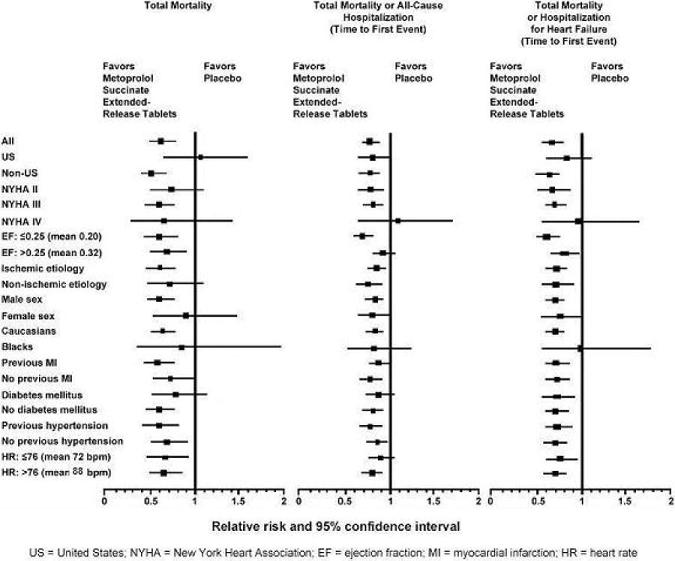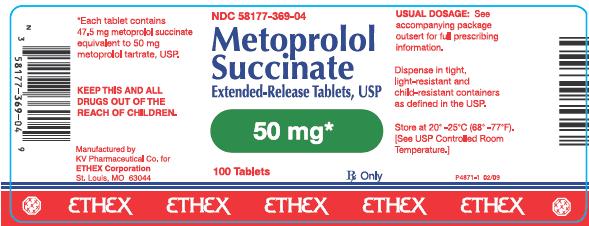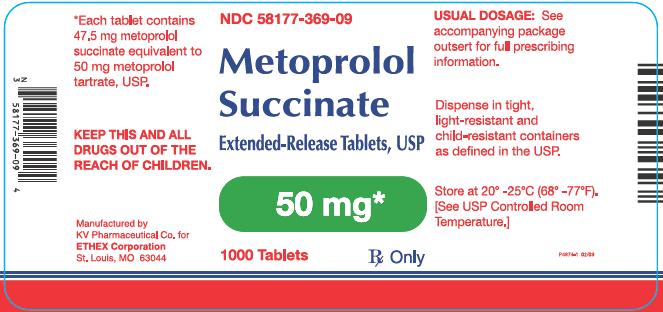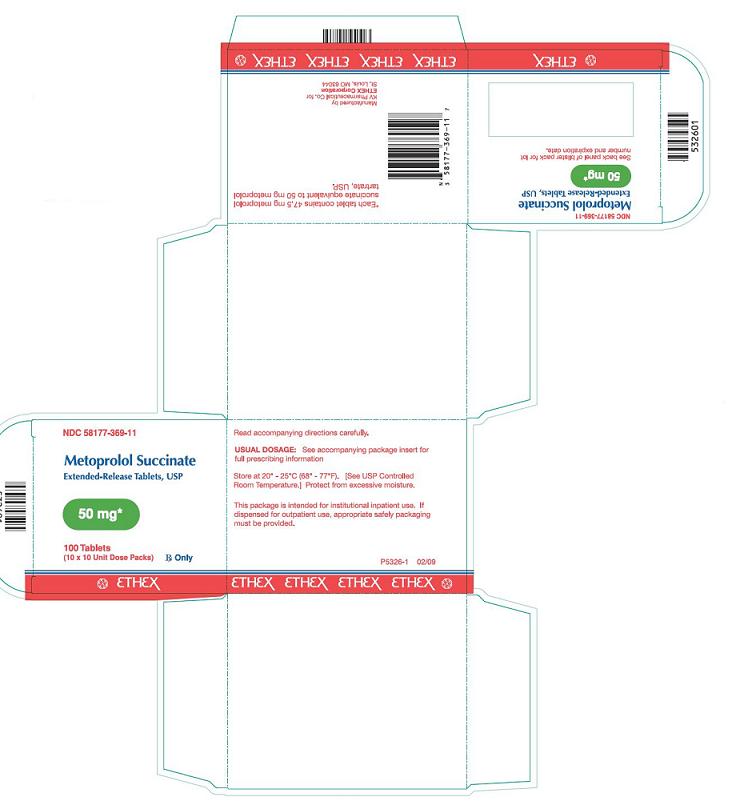 DRUG LABEL: metoprolol succinate 
NDC: 58177-369 | Form: TABLET, FILM COATED, EXTENDED RELEASE
Manufacturer: Ethex Corporation
Category: prescription | Type: HUMAN PRESCRIPTION DRUG LABEL
Date: 20100329

ACTIVE INGREDIENTS: metoprolol succinate 47.5 mg/1 1
INACTIVE INGREDIENTS: CALCIUM STEARATE; CARBOXYMETHYLCELLULOSE SODIUM; CARNAUBA WAX; CROSCARMELLOSE SODIUM; GLYCERYL BEHENATE; HYPROMELLOSE; MALTODEXTRIN; METHACRYLIC ACID - METHYL METHACRYLATE COPOLYMER (1:1); CELLULOSE, MICROCRYSTALLINE; POLYDEXTROSE; POLYETHYLENE GLYCOL; POVIDONE; SODIUM STEARYL FUMARATE; TITANIUM DIOXIDE; TRIACETIN; TRIETHYL CITRATE

Metoprolol Succinate Extended-Release Tablets, USP
50 mg

Rx Only
P4878-9 03/09

DESCRIPTION

Metoprolol succinate is a beta1-selective (cardioselective) adrenoceptor blocking agent, for oral administration, available as extended-release tablets. Metoprolol succinate extended-release tablets have been formulated to provide a controlled and predictable release of metoprolol for once daily oral administration. The tablets comprise a multiple unit system containing metoprolol succinate in a multitude of controlled-release pellets. Each pellet acts as a separate drug delivery unit and is designed to deliver metoprolol continuously over the dosage interval. The tablets contain 47.5 mg of metoprolol succinate equivalent to 50 mg of metoprolol tartrate, USP. Its chemical name is (±) 1-(isopropylamino)-3-[p-(2-methoxyethyl) phenoxy]-2-propanol succinate (2:1) (salt). Its structural formula is:

Metoprolol succinate is a white crystalline powder with a molecular weight of 652.8. It is freely soluble in water; soluble in methanol; sparingly soluble in ethanol; slightly soluble in dichloromethane and 2-propanol; practically insoluble in ethyl-acetate, acetone, diethylether and heptane. Inactive ingredients: calcium stearate, carboxymethylcellulose sodium, carnauba wax, croscarmellose sodium, glyceryl behenate, hydrogenated vegetable oil, hypromellose, maltodextrin, methacrylic acid copolymer, microcrystalline cellulose, polydextrose, polyethylene glycol, povidone, sodium stearyl fumarate, titanium dioxide, triacetin, triethyl citrate, vinyl acetate copolymer.

The USP dissolution test is pending.

CLINICAL PHARMACOLOGY

General

Metoprolol is a beta1-selective (cardioselective) adrenergic receptor blocking agent. This preferential effect is not absolute, however, and at higher plasma concentrations, metoprolol also inhibits beta2-adrenoreceptors, chiefly located in the bronchial and vascular musculature. Metoprolol has no intrinsic sympathomimetic activity, and membrane-stabilizing activity is detectable only at plasma concentrations much greater than required for beta-blockade. Animal and human experiments indicate that metoprolol slows the sinus rate and decreases AV nodal conduction.

Clinical pharmacology studies have confirmed the beta-blocking activity of metoprolol in man, as shown by (1) reduction in heart rate and cardiac output at rest and upon exercise, (2) reduction of systolic blood pressure upon exercise, (3) inhibition of isoproterenol-induced tachycardia, and (4) reduction of reflex orthostatic tachycardia.

The relative beta1-selectivity of metoprolol has been confirmed by the following: (1) In normal subjects, metoprolol is unable to reverse the beta2-mediated vasodilating effects of epinephrine. This contrasts with the effect of nonselective beta-blockers, which completely reverse the vasodilating effects of epinephrine. (2) In asthmatic patients, metoprolol reduces FEV1 and FVC significantly less than a nonselective beta-blocker, propranolol, at equivalent beta1-receptor blocking doses.

In five controlled studies in normal healthy subjects, the same daily doses of metoprolol succinate extended-release tablets and immediate-release metoprolol were compared in terms of the extent and duration of beta 1-blockade produced. Both formulations were given in a dose range equivalent to 100 to 400 mg of immediate release metoprolol per day. In these studies, metoprolol succinate extended-release tablets were administered once a day and immediate-release metoprolol was administered once to four times a day. A sixth controlled study compared the beta1- blocking effects of a 50 mg daily dose of the two formulations. In each study, beta1-blockade was expressed as the percent change from baseline in exercise heart rate following standardized submaximal exercise tolerance tests at steady state. Metoprolol succinate extended-release tablets administered once a day, and immediate-release metoprolol administered once to four times a day, provided comparable total beta1-blockade over 24 hours (area under the beta1-blockade versus time curve) in the dose range 100 to 400 mg. At a dosage of 50 mg once daily, metoprolol succinate extended-release tablets produced significantly higher total beta1-blockade over 24 hours than immediate-release metoprolol. For metoprolol succinate extended-release tablets, the percent reduction in exercise heart rate was relatively stable throughout the entire dosage interval and the level of beta1-blockade increased with increasing doses from 50 to 300 mg daily. The effects at peak/trough (i.e., at 24 hours post-dosing) were 14/9, 16/10, 24/14, 27/22 and 27/20% reduction in exercise heart rate for doses of 50, 100, 200, 300 and 400 mg metoprolol succinate extended-release tablets once a day, respectively. In contrast to metoprolol succinate extended-release tablets, immediate-release metoprolol given at a dose of 50 to 100 mg once a day produced a significantly larger peak effect on exercise tachycardia, but the effect was not evident at 24 hours. To match the peak to trough ratio obtained with metoprolol succinate extended-release tablets over the dosing range of 200 to 400 mg, a t.i.d. to q.i.d. divided dosing regimen was required for immediate-release metoprolol. A controlled crossover study in heart failure patients compared the plasma concentrations and beta1-blocking effects of 50 mg immediate-release metoprolol administered t.i.d., 100 mg and 200 mg metoprolol succinate extended-release tablets once daily. A 50 mg dose of immediate-release metoprolol t.i.d. produced a peak plasma level of metoprolol similar to the peak level observed with 200 mg of metoprolol succinate extended-release tablets. A 200 mg dose of metoprolol succinate extended-release tablets produced a larger effect on suppression of exercise-induced and Holter-monitored heart rate over 24 hours compared to 50 mg t.i.d. of immediate-release metoprolol.

The relationship between plasma metoprolol levels and reduction in exercise heart rate is independent of the pharmaceutical formulation. Using an Emax model, the maximum effect is a 30% reduction in exercise heart rate, which is attributed to beta1-blockade. Beta1-blocking effects in the range of 30 to 80% of the maximal effect (approximately 8 to 23% reduction in exercise heart rate) corresponds to metoprolol plasma concentrations from 30 to 540 nmol/L. The relative beta1-selectivity of metoprolol diminishes and blockade of beta2-adrenoceptors increases at plasma concentrations above 300 nmol/L.

Although beta-adrenergic receptor blockade is useful in the treatment of angina, hypertension, and heart failure there are situations in which sympathetic stimulation is vital. In patients with severely damaged hearts, adequate ventricular function may depend on sympathetic drive. In the presence of AV block, beta-blockade may prevent the necessary facilitating effect of sympathetic activity on conduction. Beta2-adrenergic blockade results in passive bronchial constriction by interfering with endogenous adrenergic bronchodilator activity in patients subject to bronchospasm and may also interfere with exogenous bronchodilators in such patients.

In other studies, treatment with metoprolol succinate extended-release tablets produced an improvement in left ventricular ejection fraction. Metoprolol succinate extended-release tablets were also shown to delay the increase in left ventricular end-systolic and end-diastolic volumes after 6 months of treatment.

Pharmacokinetics

Adults

In man, absorption of metoprolol is rapid and complete. Plasma levels following oral administration of conventional metoprolol tablets, however, approximate 50% of levels following intravenous administration, indicating about 50% first-pass metabolism. Metoprolol crosses the blood-brain barrier and has been reported in the CSF in a concentration 78% of the simultaneous plasma concentration.

Plasma levels achieved are highly variable after oral administration. Only a small fraction of the drug (about 12%) is bound to human serum albumin. Metoprolol is a racemic mixture of R- and S-enantiomers, and is primarily metabolized by CYP2D6. When administered orally, it exhibits stereoselective metabolism that is dependent on oxidation phenotype. Elimination is mainly by biotransformation in the liver, and the plasma half-life ranges from approximately 3 to 7 hours. Less than 5% of an oral dose of metoprolol is recovered unchanged in the urine; the rest is excreted by the kidneys as metabolites that appear to have no beta-blocking activity. Following intravenous administration of metoprolol, the urinary recovery of unchanged drug is approximately 10%. The systemic availability and half-life of metoprolol in patients with renal failure do not differ to a clinically significant degree from those in normal subjects. Consequently, no reduction in dosage is usually needed in patients with chronic renal failure.

Metoprolol is metabolized predominantly by CYP2D6, an enzyme that is absent in about 8% of Caucasians (poor metabolizers) and about 2% of most other populations. CYP2D6 can be inhibited by a number of drugs. Concomitant use of inhibiting drugs in poor metabolizers will increase blood levels of metoprolol several-fold, decreasing metoprolol's cardioselectivity (see PRECAUTIONS, Drug Interactions).

In comparison to conventional metoprolol, the plasma metoprolol levels following administration of metoprolol succinate extended-release tablets are characterized by lower peaks, longer time to peak and significantly lower peak to trough variation. The peak plasma levels following once-daily administration of metoprolol succinate extended-release tablets average one-fourth to one-half the peak plasma levels obtained following a corresponding dose of conventional metoprolol, administered once daily or in divided doses. At steady state the average bioavailability of metoprolol following administration of metoprolol succinate extended-release tablets, across the dosage range of 50 to 400 mg once daily, was 77% relative to the corresponding single or divided doses of conventional metoprolol. Nevertheless, over the 24-hour dosing interval, beta1-blockade is comparable and dose-related (see CLINICAL PHARMACOLOGY). The bioavailability of metoprolol shows a dose-related, although not directly proportional, increase with dose and is not significantly affected by food following metoprolol succinate extended-release tablets administration.

Pediatrics

Due to AstraZeneca's marketing exclusivity rights, this generic drug product is not labeled for pediatric use. Pharmacokinetic information for pediatric patients 6 to 17 years of age is approved for AstraZeneca's metoprolol succinate extended-release tablets.

Hypertension

The mechanism of the antihypertensive effects of beta-blocking agents has not been elucidated. However, several possible mechanisms have been proposed: (1) competitive antagonism of catecholamines at peripheral (especially cardiac) adrenergic neuron sites, leading to decreased cardiac output; (2) a central effect leading to reduced sympathetic outflow to the periphery; and (3) suppression of renin activity.

Clinical Trials

In a double-blind study, 1092 patients with mild-to-moderate hypertension were randomized to once daily metoprolol succinate extended-release tablets (25, 100, or 400 mg), felodipine extended-release tablets, the combination, or placebo. After 9 weeks, metoprolol succinate extended-release tablets alone decreased sitting blood pressure by 6-8/4-7 mmHg (placebo-corrected change from baseline) at 24 hours post-dose. The combination of metoprolol succinate extended-release tablets with felodipine extended-release tablets has greater effects on blood pressure.

In controlled clinical studies, an immediate-release dosage form of metoprolol was an effective antihypertensive agent when used alone or as concomitant therapy with thiazide-type diuretics at dosages of 100 to 450 mg daily. Metoprolol succinate extended-release tablets, in dosages of 100 to 400 mg once daily, produces similar beta1-blockade as conventional metoprolol tablets administered two to four times daily. In addition, metoprolol succinate extended-release tablets administered at a dose of 50 mg once daily lowered blood pressure 24 hours post-dosing in placebo-controlled studies. In controlled, comparative, clinical studies, immediate-release metoprolol appeared comparable as an antihypertensive agent to propranolol, methyldopa, and thiazide-type diuretics, and affected both supine and standing blood pressure. Because of variable plasma levels attained with a given dose and lack of a consistent relationship of antihypertensive activity to drug plasma concentration, selection of proper dosage requires individual titration.

Angina Pectoris

By blocking catecholamine-induced increases in heart rate, in velocity and extent of myocardial contraction, and in blood pressure, metoprolol reduces the oxygen requirements of the heart at any given level of effort, thus making it useful in the long- term management of angina pectoris.

Clinical Trials

In controlled clinical trials, an immediate-release formulation of metoprolol has been shown to be an effective antianginal agent, reducing the number of angina attacks and increasing exercise tolerance. The dosage used in these studies ranged from 100 to 400 mg daily. Metoprolol succinate extended-release tablets, in dosages of 100 to 400 mg once daily, has been shown to possess beta-blockade similar to conventional metoprolol tablets administered two to four times daily.

Heart Failure

The precise mechanism for the beneficial effects of beta-blockers in heart failure has not been elucidated.

Clinical Trials

MERIT-HF was a double-blind, placebo-controlled study of metoprolol succinate extended-release tablets conducted in 14 countries including the U.S. It randomized 3991 patients (1990 to metoprolol succinate extended-release tablets) with ejection fraction ≤0.40 and NYHA Class II-IV heart failure attributable to ischemia, hypertension, or cardiomyopathy. The protocol excluded patients with contraindications to beta-blocker use, those expected to undergo heart surgery, and those within 28 days of myocardial infarction or unstable angina. The primary endpoints of the trial were (1) all-cause mortality plus all-cause hospitalization (time to first event) and (2) all-cause mortality. Patients were stabilized on optimal concomitant therapy for heart failure, including diuretics, ACE inhibitors, cardiac glycosides, and nitrates. At randomization, 41% of patients were NYHA Class II, 55% NYHA Class III; 65% of patients had heart failure attributed to ischemic heart disease; 44% had a history of hypertension; 25% had diabetes mellitus; 48% had a history of myocardial infarction. Among patients in the trial, 90% were on diuretics, 89% were on ACE inhibitors, 64% were on digitalis, 27% were on a lipid-lowering agent, 37% were on an oral anticoagulant, and the mean ejection fraction was 0.28. The mean duration of follow-up was one year. At the end of the study, the mean daily dose of metoprolol succinate extended-release tablets was 159 mg.

The trial was terminated early for a statistically significant reduction in all-cause mortality (34%, nominal p=0.00009). The risk of all-cause mortality plus all-cause hospitalization was reduced by 19% (p=0.00012). The trial also showed improvements in heart failure-related mortality and heart failure-related hospitalizations, and NYHA functional class.

The table below shows the principal results for the overall study population. The figure below illustrates principal results for a wide variety of subgroup comparisons, including U.S. vs. non-U.S. populations (the latter of which was not pre-specified). The combined endpoints of all-cause mortality plus all-cause hospitalization and of mortality plus heart failure hospitalization showed consistent effects in the overall study population and the subgroups, including women and the U.S. population. However, in the U.S. subgroup (n=1071) and women (n=898), overall mortality and cardiovascular mortality appeared less affected. Analyses of female and U.S. patients were carried out because they each represented about 25% of the overall population. Nonetheless, subgroup analyses can be difficult to interpret and it is not known whether these represent true differences or chance effects.

Clinical Endpoints in the MERIT-HF Study
Clinical Endpoint | Number of Patients |  | Relative Risk (95% CI) | Risk Reduction with Metoprolol Succinate Extended-release tablets | Nominal P-value
Clinical Endpoint | Placebo n=2001 | Metoprolol Succinate Extended-release tablets n=1990 | Relative Risk (95% CI) | Risk Reduction with Metoprolol Succinate Extended-release tablets | Nominal P-value
All-cause mortality plus all-cause hospitalization† | 767 | 641 | 0.81 (0.73-0.90) | 19% | 0.00012
All-cause mortality | 217 | 145 | 0.66 (0.53-0.81) | 34% | 0.00009
All-cause mortality plus heart failure hospitalization† | 439 | 311 | 0.69 (0.60-0.80) | 31% | 0.0000008
Cardiovascular mortality | 203 | 128 | 0.62 (0.50-0.78) | 38% | 0.000022
Sudden death | 132 | 79 | 0.59 (0.45-0.78) | 41% | 0.0002
Death due to worsening heart failure | 58 | 30 | 0.51 (0.33-0.79) | 49% | 0.0023
Hospitalizations due to worsening heart failure‡ | 451 | 317 | N/A | N/A | 0.0000076
Cardiovascular hospitalization‡ | 773 | 649 | N/A | N/A | 0.00028
† Time to first event
‡ Comparison of treatment groups examines the number of hospitalizations (Wilcoxon test); relative risk and risk reduction are not applicable.

Results for Subgroups in MERIT-HF

INDICATIONS AND USAGE

Hypertension

Metoprolol succinate extended-release tablets are indicated for the treatment of hypertension. It may be used alone or in combination with other antihypertensive agents.

Angina Pectoris

Metoprolol succinate extended-release tablets are indicated in the long-term treatment of angina pectoris.

Heart Failure

Metoprolol succinate extended-release tablets are indicated for the treatment of stable, symptomatic (NYHA Class II or III) heart failure of ischemic, hypertensive, or cardiomyopathic origin. It was studied in patients already receiving ACE inhibitors, diuretics, and, in the majority of cases, digitalis. In this population, metoprolol succinate extended-release tablets decreased the rate of mortality plus hospitalization, largely through a reduction in cardiovascular mortality and hospitalizations for heart failure.

CONTRAINDICATIONS

Metoprolol succinate extended-release tablets are contraindicated in severe bradycardia, heart block greater than first degree, cardiogenic shock, decompensated cardiac failure, sick sinus syndrome (unless a permanent pacemaker is in place), and in patients who are hypersensitive to any component of this product.

WARNINGS

BOXED WARNING

Ischemic Heart Disease: Following abrupt cessation of therapy with certain beta-blocking agents, exacerbations of angina pectoris and, in some cases, myocardial infarction have occurred. When discontinuing chronically administered metoprolol succinate extended-release tablets, particularly in patients with ischemic heart disease, the dosage should be gradually reduced over a period of 1 to 2 weeks and the patient should be carefully monitored. If angina markedly worsens or acute coronary insufficiency develops, metoprolol succinate extended-release tablets administration should be reinstated promptly, at least temporarily, and other measures appropriate for the management of unstable angina should be taken. Patients should be warned against interruption or discontinuation of therapy without the physician's advice. Because coronary artery disease is common and may be unrecognized, it may be prudent not to discontinue metoprolol succinate extended-release tablets therapy abruptly even in patients treated only for hypertension.

Bronchospastic Diseases: PATIENTS WITH BRONCHOSPASTIC DISEASES SHOULD, IN GENERAL, NOT RECEIVE BETA-BLOCKERS. Because of its relative beta1-selectivity, however, metoprolol succinate extended-release tablets may be used with caution in patients with bronchospastic disease who do not respond to, or cannot tolerate, other antihypertensive treatment. Since beta1-selectivity is not absolute, a beta2-stimulating agent should be administered concomitantly, and the lowest possible dose of metoprolol succinate extended-release tablets should be used (see DOSAGE AND ADMINISTRATION).

Pheochromocytoma: If metoprolol succinate extended-release tablets are used in the setting of pheochromocytoma, it should be given in combination with an alpha blocker, and only after the alpha blocker has been initiated. Administration of beta blockers alone in the setting of pheochromocytoma has been associated with a paradoxical increase in blood pressure due to the attenuation of beta-mediated vasodilatation in skeletal muscle.

Major Surgery: The necessity or desirability of withdrawing beta-blocking therapy prior to major surgery is controversial; the impaired ability of the heart to respond to reflex adrenergic stimuli may augment the risks of general anesthesia and surgical procedures.

Metoprolol succinate extended-release tablets, like other beta-blockers, is a competitive inhibitor of beta-receptor agonists, and its effects can be reversed by administration of such agents, e.g., dobutamine or isoproterenol. However, such patients may be subject to protracted severe hypotension. Difficulty in restarting and maintaining the heart beat has also been reported with beta-blockers.

Diabetes and Hypoglycemia: Metoprolol succinate extended-release tablets should be used with caution in diabetic patients if a beta-blocking agent is required. Beta-blockers may mask tachycardia occurring with hypoglycemia, but other manifestations such as dizziness and sweating may not be significantly affected.

Thyrotoxicosis: Beta-adrenergic blockade may mask certain clinical signs (e.g., tachycardia) of hyperthyroidism. Patients suspected of developing thyrotoxicosis should be managed carefully to avoid abrupt withdrawal of beta-blockade, which might precipitate a thyroid storm.

Peripheral Vascular Disease: Beta-blockers can precipitate or aggravate symptoms of arterial insufficiency in patients with peripheral vascular disease. Caution should be exercised in such individuals.

Calcium Channel Blockers: Because of significant inotropic and chronotropic effects in patients treated with beta-blockers and calcium channel blockers of the verapamil and diltiazem type, caution should be exercised in patients treated with these agents concomitantly.

PRECAUTIONS

General

Metoprolol succinate extended-release tablets should be used with caution in patients with impaired hepatic function. In patients with pheochromocytoma, an alpha-blocking agent should be initiated prior to the use of any beta-blocking agent (see WARNINGS).

Worsening cardiac failure may occur during up-titration of metoprolol succinate extended-release tablets. If such symptoms occur, diuretics should be increased and the dose of metoprolol succinate extended-release tablets should not be advanced until clinical stability is restored (see DOSAGE AND ADMINISTRATION). It may be necessary to lower the dose of metoprolol succinate extended-release tablets or temporarily discontinue it. Such episodes do not preclude subsequent successful titration of metoprolol succinate extended-release tablets.

Information for Patients

Patients should be advised to take metoprolol succinate regularly and continuously, as directed, preferably with or immediately following meals. If a dose should be missed, the patient should take only the next scheduled dose (without doubling it). Patients should not interrupt or discontinue metoprolol succinate extended-release tablets without consulting the physician.

Patients should be advised (1) to avoid operating automobiles and machinery or engaging in other tasks requiring alertness until the patient 's response to therapy with metoprolol succinate extended-release tablets has been determined; (2) to contact the physician if any difficulty in breathing occurs; (3) to inform the physician or dentist before any type of surgery that he or she is taking metoprolol succinate extended-release tablets.

Heart failure patients should be advised to consult their physician if they experience signs or symptoms of worsening heart failure such as weight gain or increasing shortness of breath.

Laboratory Tests

Clinical laboratory findings may include elevated levels of serum transaminase, alkaline phosphatase, and lactate dehydrogenase.

Drug Interactions

Catecholamine-depleting drugs (e.g., reserpine, monoamine oxidase (MAO) inhibitors) may have an additive effect when given with beta-blocking agents. Patients treated with metoprolol succinate extended-release tablets plus a catecholamine depletor should therefore be closely observed for evidence of hypotension or marked bradycardia, which may produce vertigo, syncope, or postural hypotension.

Drugs that inhibit CYP2D6 such as quinidine, fluoxetine, paroxetine, and propafenone are likely to increase metoprolol concentration. In healthy subjects with CYP2D6 extensive metabolizer phenotype, coadministration of quinidine 100 mg and immediate release metoprolol 200 mg tripled the concentration of S-metoprolol and doubled the metoprolol elimination half-life. In four patients with cardiovascular disease, coadministration of propafenone 150 mg t.i.d. with immediate-release metoprolol 50 mg t.i.d. resulted in two- to five-fold increases in the steady-state concentration of metoprolol. These increases in plasma concentration would decrease the cardioselectivity of metoprolol.

Both digitalis glycosides and beta-blockers slow atrioventricular conduction and decrease heart rate. Concomitant use can increase the risk of bradycardia.

Beta-blockers may exacerbate the rebound hypertension which can follow the withdrawal of clonidine. If the two drugs are coadministered, the beta blocker should be withdrawn several days before the gradual withdrawal of clonidine. If replacing clonidine by beta-blocker therapy, the introduction of beta-blockers should be delayed for several days after clonidine administration has stopped.

Carcinogenesis, Mutagenesis, Impairment of Fertility

Long-term studies in animals have been conducted to evaluate the carcinogenic potential of metoprolol tartrate. In 2-year studies in rats at three oral dosage levels of up to 800 mg/kg/day (41 times, on a mg/m^2 basis, the daily dose of 200 mg for a 60-kg patient), there was no increase in the development of spontaneously occurring benign or malignant neoplasms of any type. The only histologic changes that appeared to be drug related were an increased incidence of generally mild focal accumulation of foamy macrophages in pulmonary alveoli and a slight increase in biliary hyperplasia. In a 21-month study in Swiss albino mice at three oral dosage levels of up to 750 mg/kg/day (18 times, on a mg/m^2 basis, the daily dose of 200 mg for a 60-kg patient), benign lung tumors (small adenomas) occurred more frequently in female mice receiving the highest dose than in untreated control animals. There was no increase in malignant or total (benign plus malignant) lung tumors, nor in the overall incidence of tumors or malignant tumors. This 21-month study was repeated in CD-1 mice, and no statistically or biologically significant differences were observed between treated and control mice of either sex for any type of tumor.

All genotoxicity tests performed on metoprolol tartrate (a dominant lethal study in mice, chromosome studies in somatic cells, a Salmonella/mammalian-microsome mutagenicity test, and a nucleus anomaly test in somatic interphase nuclei) and metoprolol succinate (a Salmonella/mammalian-microsome mutagenicity test) were negative.

No evidence of impaired fertility due to metoprolol tartrate was observed in a study performed in rats at doses up to 22 times, on a mg/m^2 basis, the daily dose of 200 mg in a 60-kg patient.

Pregnancy Category C

Metoprolol tartrate has been shown to increase post-implantation loss and decrease neonatal survival in rats at doses up to 22 times, on a mg/m^2 basis, the daily dose of 200 mg in a 60 kg patient. Distribution studies in mice confirm exposure of the fetus when metoprolol tartrate is administered to the pregnant animal. These studies have revealed no evidence of impaired fertility or teratogenicity. There are no adequate and well-controlled studies in pregnant women. Because animal reproduction studies are not always predictive of human response, this drug should be used during pregnancy only if clearly needed.

Nursing Mothers

Metoprolol is excreted in breast milk in very small quantities. An infant consuming 1 liter of breast milk daily would receive a dose of less than 1 mg of the drug. Caution should be exercised when metoprolol succinate extended-release tablets is administered to a nursing woman.

Pediatric Use

Safety and effectiveness of metoprolol succinate have not been established in patients < 6 years of age. Due to AstraZeneca's marketing exclusivity rights, this generic drug product is not labeled for pediatric use. Pediatric use information is approved for AstraZeneca's metoprolol succinate extended-release tablets.

Geriatric Use

Clinical studies of metoprolol succinate extended-release tablets in hypertension did not include sufficient numbers of subjects aged 65 and over to determine whether they respond differently from younger subjects. Other reported clinical experience in hypertensive patients has not identified differences in responses between elderly and younger patients.

Of the 1,990 patients with heart failure randomized to metoprolol succinate extended-release tablets in the MERIT-HF trial, 50% (990) were 65 years of age and older and 12% (238) were 75 years of age and older. There were no notable differences in efficacy or the rate of adverse events between older and younger patients.

In general, dose selection for an elderly patient should be cautious, usually starting at the low end of the dosing range, reflecting greater frequency of decreased hepatic, renal, or cardiac function, and of concomitant disease or other drug therapy.

Risk of Anaphylactic Reactions

While taking beta-blockers, patients with a history of severe anaphylactic reactions to a variety of allergens may be more reactive to repeated challenge, either accidental, diagnostic or therapeutic. Such patients may be unresponsive to the usual doses of epinephrine used to treat allergic reaction.

ADVERSE REACTIONS

Hypertension and Angina

Most adverse effects have been mild and transient. The following adverse reactions have been reported for immediate release metoprolol tartrate.

Central Nervous System: Tiredness and dizziness have occurred in about 10 of 100 patients. Depression has been reported in about 5 of 100 patients. Mental confusion and short- term memory loss have been reported. Headache, somnolence, nightmares, and insomnia have also been reported.

Cardiovascular: Shortness of breath and bradycardia have occurred in approximately 3 of 100 patients. Cold extremities; arterial insufficiency, usually of the Raynaud type; palpitations; congestive heart failure; peripheral edema; syncope; chest pain; and hypotension have been reported in about 1 of 100 patients (see CONTRAINDICATIONS, WARNINGS, and PRECAUTIONS).

Respiratory: Wheezing (bronchospasm) and dyspnea have been reported in about 1 of 100 patients (see WARNINGS).

Gastrointestinal: Diarrhea has occurred in about 5 of 100 patients. Nausea, dry mouth, gastric pain, constipation, flatulence, digestive tract disorders and heartburn have been reported in about 1 of 100 patients.

Hypersensitive Reactions: Pruritus or rash have occurred in about 5 of 100 patients. Worsening of psoriasis has also been reported.

Miscellaneous: Peyronie's disease has been reported in fewer than 1 of 100,000 patients. Musculoskeletal pain, blurred vision, decreased libido, and tinnitus have also been reported.

There have been rare reports of reversible alopecia, agranulocytosis, and dry eyes. Discontinuation of the drug should be considered if any such reaction is not otherwise explicable. The oculomucocutaneous syndrome associated with the beta-blocker practolol has not been reported with metoprolol.

Potential Adverse Reactions

In addition, there are a variety of adverse reactions not listed above which have been reported with other beta-adrenergic blocking agents and should be considered potential adverse reactions to metoprolol succinate.

Central Nervous System: Reversible mental depression progressing to catatonia; an acute reversible syndrome characterized by disorientation for time and place, short-term memory loss, emotional lability, slightly clouded sensorium, and decreased performance on neuropsychometrics.

Cardiovascular: Intensification of AV block (see CONTRAINDICATIONS).

Hematologic: Agranulocytosis, nonthrombocytopenic purpura, thrombocytopenic purpura.

Hypersensitive Reactions: Fever combined with aching and sore throat, laryngospasm, and respiratory distress.

Heart Failure

In the MERIT-HF study, serious adverse events and adverse events leading to discontinuation of study medication were systematically collected. In the MERIT-HF study comparing metoprolol succinate extended-release tablets in daily doses up to 200 mg (mean dose 159 mg once-daily) (n=1990) to placebo (n=2001), 10.3% of metoprolol succinate extended-release tablets patients discontinued for adverse events vs. 12.2% of placebo patients.

The table below lists adverse events in the MERIT-HF study that occurred at an incidence of equal to or greater than 1% in the metoprolol succinate extended-release tablets group and greater than placebo by more than 0.5%, regardless of the assessment of causality.

Adverse Events Occurring in the MERIT-HF Study at an Incidence ≥ 1% in the Metoprolol Succinate Extended-Release Tablets Group and Greater than Placebo by More Than 0.5%
 | Metoprolol Succinate Extended-Release Tablets N=1990 % of patients | Placebo N=2001 % of patients
Dizziness/vertigo | 1.8 | 1.0
Bradycardia | 1.5 | 0.4
Accident and/or injury | 1.4 | 0.8

Other adverse events with an incidence of >1% on metoprolol succinate extended-release tablets and as common on placebo (within 0.5%) included myocardial infarction, pneumonia, cerebrovascular disorder, chest pain, dyspnea/dyspnea aggravated, syncope, coronary artery disorder, ventricular tachycardia/arrhythmia aggravated, hypotension, diabetes mellitus/diabetes mellitus aggravated, abdominal pain, and fatigue.

Postmarketing Experience

The following adverse reactions have been reported with metoprolol succinate extended-release tablets in worldwide postmarketing use, regardless of causality:

Cardiovascular: 2nd and 3rd degree heart block, cardiogenic shock in patients with acute myocardial infarction.

Gastrointestinal: hepatitis, vomiting.

Hematologic: thrombocytopenia.

Musculoskeletal: arthralgia.

Nervous System/Psychiatric: anxiety/nervousness, hallucinations, paresthesia.

Reproductive, male: impotence.

Skin: increased sweating, photosensitivity, urticaria.

Special Sense Organs: taste disturbances.

OVERDOSAGE

Acute Toxicity

There have been a few reports of overdosage with metoprolol succinate extended-release tablets and no specific overdosage information was obtained with this drug, with the exception of animal toxicology data. However, since metoprolol succinate extended-release tablets (metoprolol succinate salt) contain the same active moiety, metoprolol, as conventional metoprolol tablets (metoprolol tartrate salt), the recommendations on overdosage for metoprolol conventional tablets are applicable to metoprolol succinate extended-release tablets.

Signs and Symptoms

Overdosage of metoprolol succinate extended-release tablets may lead to severe hypotension, sinus bradycardia, atrioventricular block, heart failure, cardiogenic shock, cardiac arrest, bronchospasm, impairment of consciousness/coma, nausea, vomiting, and cyanosis.

Treatment

In general, patients with acute or recent myocardial infarction or congestive heart failure may be more hemodynamically unstable than other patients and should be treated accordingly. When possible the patient should be treated under intensive care conditions. On the basis of the pharmacologic actions of metoprolol, the following general measures should be employed:

Elimination of the Drug: Gastric lavage should be performed.

Bradycardia: Atropine should be given intravenously. If the response is inadequate, isoproterenol or any other agent with positive chronotropic properties may be given cautiously. Under some circumstances, transvenous pacemaker insertion may be necessary.

Hypotension: A vasopressor should be administered, e.g., levarterenol or dopamine.

Bronchospasm: A beta2-stimulating agent and/or a theophylline derivative should be administered.

Cardiac Failure: A digitalis glycoside and diuretics should be administered. In shock resulting from inadequate cardiac contractility, administration of dobutamine, isoproterenol or glucagon may be considered.

DOSAGE AND ADMINISTRATION

Metoprolol succinate extended-release tablets are intended for once daily administration. For treatment of hypertension and angina, when switching from immediate-release metoprolol to metoprolol succinate extended-release tablets, the same total daily dose of metoprolol succinate extended-release tablets should be used. Dosages of metoprolol succinate extended-release tablets should be individualized and titration may be needed in some patients.

Metoprolol succinate extended-release tablets are scored and can be divided; however, the whole or half tablet should be swallowed whole and not chewed or crushed.

Hypertension

The usual initial dosage is 25 to 100 mg daily in a single dose, whether used alone or added to a diuretic. The dosage may be increased at weekly (or longer) intervals until optimum blood pressure reduction is achieved. In general, the maximum effect of any given dosage level will be apparent after 1 week of therapy. Dosages above 400 mg per day have not been studied.

Due to AstraZeneca's marketing exclusivity rights, this generic drug product is not labeled for pediatric use. Dosage and administration information in pediatric patients 6 years and older is approved for AstraZeneca's metoprolol succinate extended-release tablets.

Angina Pectoris

The dosage of metoprolol succinate extended-release tablets should be individualized. The usual initial dosage is 100 mg daily, given in a single dose. The dosage may be gradually increased at weekly intervals until optimum clinical response has been obtained or there is a pronounced slowing of the heart rate. Dosages above 400 mg per day have not been studied. If treatment is to be discontinued, the dosage should be reduced gradually over a period of 1 to 2 weeks (see WARNINGS).

Heart Failure

Dosage must be individualized and closely monitored during up-titration. Prior to initiation of metoprolol succinate extended-release tablets, the dosing of diuretics, ACE inhibitors, and digitalis (if used) should be stabilized. The recommended starting dose of metoprolol succinate extended-release tablets is 25 mg once daily for two weeks in patients with NYHA Class II heart failure and 12.5 mg once daily in patients with more severe heart failure. The dose should then be doubled every two weeks to the highest dosage level tolerated by the patient or up to 200 mg of metoprolol succinate extended-release tablets. If transient worsening of heart failure occurs, it may be treated with increased doses of diuretics, and it may also be necessary to lower the dose of metoprolol succinate extended-release tablets or temporarily discontinue it. The dose of metoprolol succinate extended-release tablets should not be increased until symptoms of worsening heart failure have been stabilized. Initial difficulty with titration should not preclude later attempts to introduce metoprolol succinate extended-release tablets. If heart failure patients experience symptomatic bradycardia, the dose of metoprolol succinate extended-release tablets should be reduced.

HOW SUPPLIED

Metoprolol succinate extended-release tablets for oral administration are supplied as follows:

50 mg: White, lightly mottled, film-coated round tablets containing 47.5 mg of metoprolol succinate equivalent to 50 mg of metoprolol tartrate, USP and debossed “369” on one side with a bisect on the other side.

NDC 58177-369-04………………….…Bottles of 100

NDC 58177-369-09………………….…Bottles of 1000

NDC 58177-369-11………………….…Packages of 100 (10 x 10 cards)

Store at 20°-25°C (68°-77°F). [See USP Controlled Room Temperature.]

Manufactured by
KV Pharmaceutical Co. for
ETHEX Corporation
St. Louis, MO 63044

P4878-9
03/09

100 Tablets Bottle Label

NDC 58177-369-04

Metorpolol Succinate

Extended-Release Tablets, USP

50 mg*

100 Tablets

Rx Only

ETHEX

1000 Tablets Bottle Label

NDC 58177-369-09

Metorpolol Succinate

Extended-Release Tablets, USP

50 mg*

1000 Tablets

Rx Only

ETHEX

100 Tablets Blister Pack Label

NDC 58177-369-11

Metorpolol Succinate

Extended-Release Tablets, USP

50 mg*

100 Tablets

(10 x 10 Unit Dose Packs)

Rx Only

ETHEX